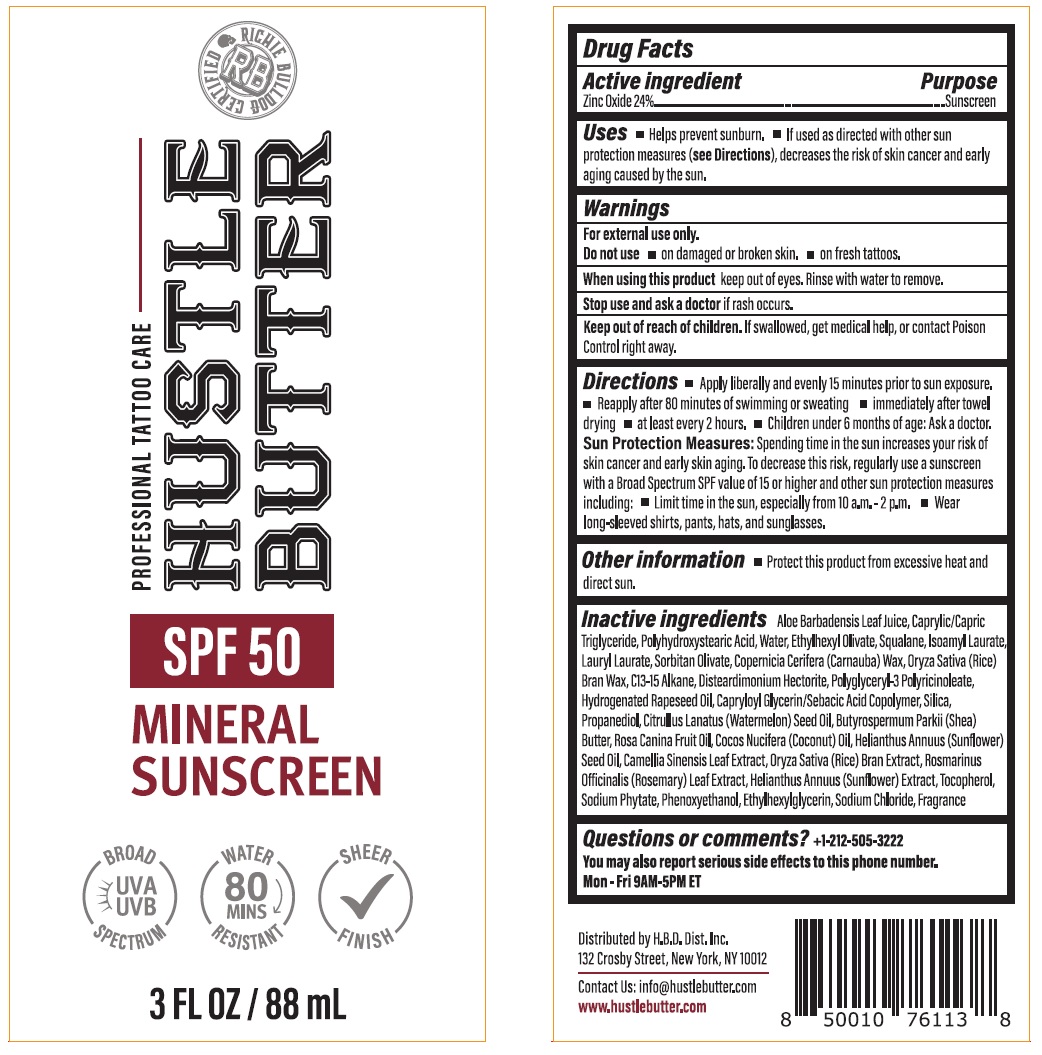 DRUG LABEL: HUSTLE BUTTER SPF 50 MINERAL SUNSCREEN
NDC: 72014-201 | Form: LOTION
Manufacturer: H.B.D. DIST. INC.
Category: otc | Type: HUMAN OTC DRUG LABEL
Date: 20250310

ACTIVE INGREDIENTS: ZINC OXIDE 24 g/100 mL
INACTIVE INGREDIENTS: ALOE VERA LEAF; MEDIUM-CHAIN TRIGLYCERIDES; POLYHYDROXYSTEARIC ACID STEARATE; WATER; ETHYLHEXYL OLIVATE; SQUALANE; ISOAMYL LAURATE; LAURYL LAURATE; SORBITAN OLIVATE; CARNAUBA WAX; RICE BRAN; C13-15 ALKANE; DISTEARDIMONIUM HECTORITE; POLYGLYCERYL-3 PENTARICINOLEATE; HYDROGENATED RAPESEED OIL; CAPRYLOYL GLYCERIN/SEBACIC ACID COPOLYMER (2000 MPA.S); SILICON DIOXIDE; PROPANEDIOL; WATERMELON SEED OIL; SHEA BUTTER; ROSA CANINA FRUIT OIL; COCONUT OIL; SUNFLOWER OIL; GREEN TEA LEAF; ROSEMARY; HELIANTHUS ANNUUS FLOWERING TOP; TOCOPHEROL; PHYTATE SODIUM; PHENOXYETHANOL; ETHYLHEXYLGLYCERIN; SODIUM CHLORIDE

HUSTLE BUTTER SPF 50 MINERAL SUNSCREEN

Active ingredient

Zinc Oxide 24%

Purpose

Sunscreen

Uses

• Helps prevent sunburn. • If used as directed with other sun protection measures (see Directions), decreases the risk of skin cancer and early aging caused by the sun.

Warnings

For external use only.

Do not use • on damaged or broken skin. • on fresh tattoos.

When using this product keep out of eyes. Rinse with water to remove.

Stop use and ask a doctor if rash occurs.

Keep out of reach of children. If swallowed, get medical help, or contact Poison Control right away.

Directions

• Apply liberally and evenly 15 minutes prior to sun exposure. • Reapply after 80 minutes of swimming or sweating • immediately after towel drying • at least every 2 hours. • Children under 6 months of age: Ask a doctor. Sun Protection Measures: Spending time in the sun increases your risk of skin cancer and early skin aging. To decrease this risk, regularly use a sunscreen with a Broad Spectrum SPF value of 15 or higher and other sun protection measures including: • Limit time in the sun, especially from 10 a.m.-2 p.m. • Wear long-sleeved shirts, pants, hats, and sunglasses.

Other information

• Protect this product from excessive heat and direct sun.

Inactive ingredients

Aloe Barbadensis Leaf Juice, Caprylic/Capric Triglyceride, Polyhydroxystearic Acid, Water, Ethylhexyl Olivate, Squalane, Isoamyl Laurate, Lauryl Laurate, Sorbitan Olivate, Copernicia Cerifera (Carnauba) Wax, Oryza Sativa (Rice) Bran Wax, C13-15 Alkane, Disteardimonium Hectorite, Polyglyceryl-3 Polyricinoleate, Hydrogenated Rapeseed Oil, Capryloyl Glycerin/Sebacic Acid Copolymer, Silica, Propanediol, Citrullus Lanatus (Watermelon) Seed Oil, Butyrospermum Parkii (Shea) Butter, Rosa Canina Fruit Oil, Cocos Nucifera (Coconut) Oil, Helianthus Annuus (Sunflower) Seed Oil, Camellia Sinensis Leaf Extract, Oryza Sativa (Rice) Bran Extract, Rosmarinus Officinalis (Rosemary) Leaf Extract, Helianthus Annuus (Sunflower) Extract, Tocopherol, Sodium Phytate, Phenoxyethanol, Ethylhexylglycerin, Sodium Chloride, Fragrance

Questions or comments?

+1-212-505-3222

You may also report serious side effects to this phone number.

Mon-Fri 9AM-5PM ET

PROFESSIONAL TATTOO CARE

BROAD SPECTRUM UVA UVB

WATER RESISTANT 80 MINS

SHEER FINISH

Distributed by H.B.D. Dist. Inc.
132 Crosby Street, New York, NY 10012

Contact Us: info@hustlebutter.com
www. hustlebutter.com